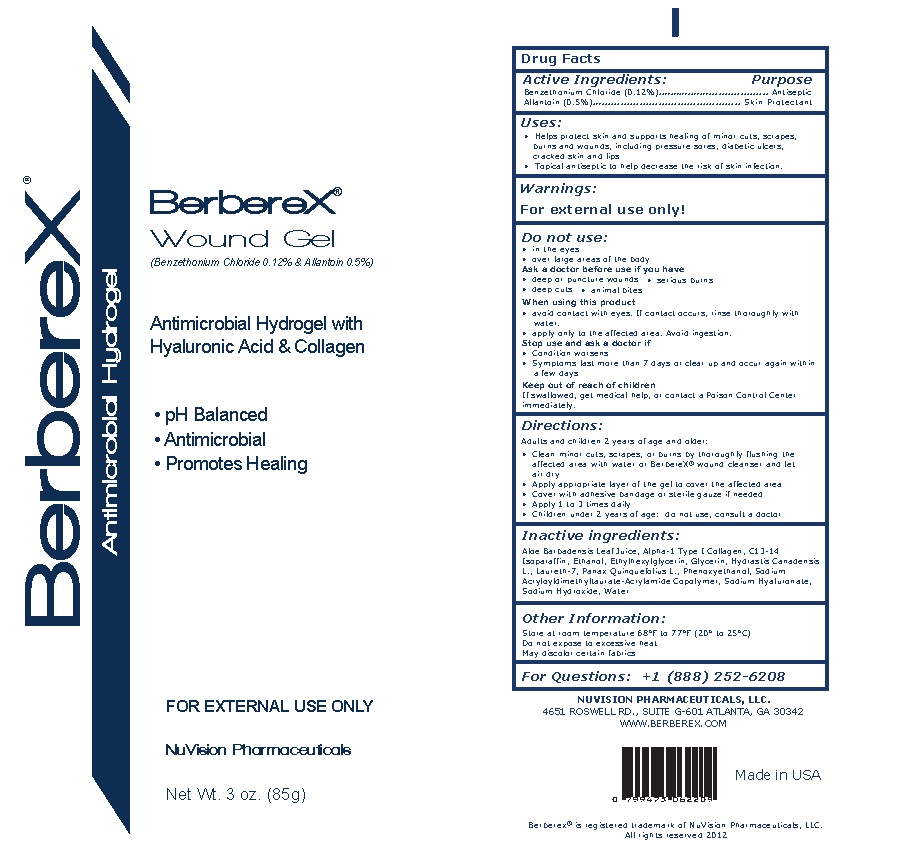 DRUG LABEL: Berberex Wound Gel
NDC: 52261-0601 | Form: GEL
Manufacturer: Cosco International, Inc.
Category: otc | Type: HUMAN OTC DRUG LABEL
Date: 20250328

ACTIVE INGREDIENTS: BENZETHONIUM CHLORIDE 0.0012 kg/1 kg; ALLANTOIN 0.0050 kg/1 kg
INACTIVE INGREDIENTS: ALOE VERA LEAF; HYDROLYSED BOVINE COLLAGEN (ENZYMATIC; 2000-5000 MW); C13-14 ISOPARAFFIN; ALCOHOL; ETHYLHEXYLGLYCERIN; GLYCERIN; HYDRASTIS CANADENSIS WHOLE; LAURETH-7; PANAX QUINQUEFOLIUS WHOLE; PHENOXYETHANOL; SODIUM ACRYLOYLDIMETHYLTAURATE-ACRYLAMIDE COPOLYMER (1:1; 90000-150000 MPA.S); HYALURONATE SODIUM; SODIUM HYDROXIDE; WATER

BerbereX Wound Gel - Antimicrobial Skin & Wound Hydrogel

DRUG FACTS

Active Ingredient/Purpose:

Benzethonium Chloride (0.12%)..............Antiseptic

Allantoin (0.5%)...............................Skin Protectant

Uses:

Helps protect skin and supports healing of minor cuts, scrapes, burns and wounds, including pressure sores, diabetic ulcers, cracked skin, and lips. Topical antiseptic to help decrease the risk of infection

Warnings:

For external use only.

Do not use:

• in the eyes
• over large areas of the body

Ask a doctor before use if you have:

• deep or puncture wounds
• deep cuts
• animal bites
• serious burns

When using this product:

• Avoid contact with eyes. If contact occurs, rinse thoroughly with water.
• Apply only to the affected area. Avoid ingestion.

Stop use and ask a doctor if:

• Condition worsens
• Symptoms last more than 7 days or clear up and occur again within a few days

Keep out of reach of children.

• If swallowed, get medical help or contact a Poison Control Center immediately.

Directions:

Adults and children 2 years of age and older:
• Clean minor cut, scrapes, or burns by thoroughly flushing the affected area with water or BerbereX® wound cleanser and let air dry
• Apply appropriate layer of the gel to cover the affected area
• Cover with adhesive bandage or sterile gauze if needed
• Apply 1 to 3 times daily
• Children under 2 years of age: ask a doctor

Inactive Ingredients:

Aloe Barbadensis Leaf Juice, C13-14 Isoparaffin, Ethanol, Ethylhexylglycerin, Glycerin, Hydrastis Canadensis L., Hydrolyzed Bovine Collagen, Laureth-7, Panax Quinquefolius L., Phenoxyethanol, Sodium Acryloyldimethyltaurate-Acrylamide Copolymer, Sodium Hyaluronate, Sodium Hydroxide, Water

Storage and handling:

Store at room temperature 68°F to 77°F (20° to 25°C)
Do not expose to excessive heat
May discolor or stain certain fabrics

For Questions:

Call 1-888-252-6208
NuVision Pharmaceuticals, LLC.
4651 Roswell Rd., Suite G-601
Atlanta, GA 30342
Website: www.berberex.com